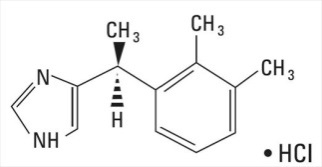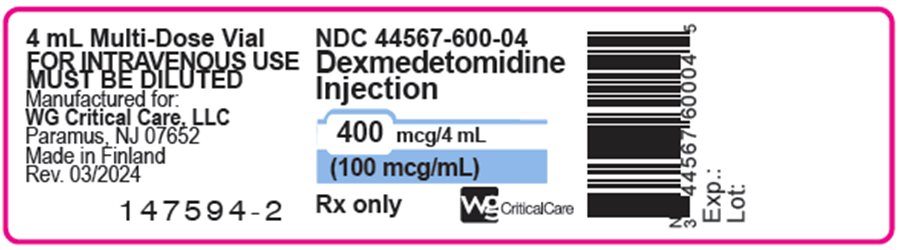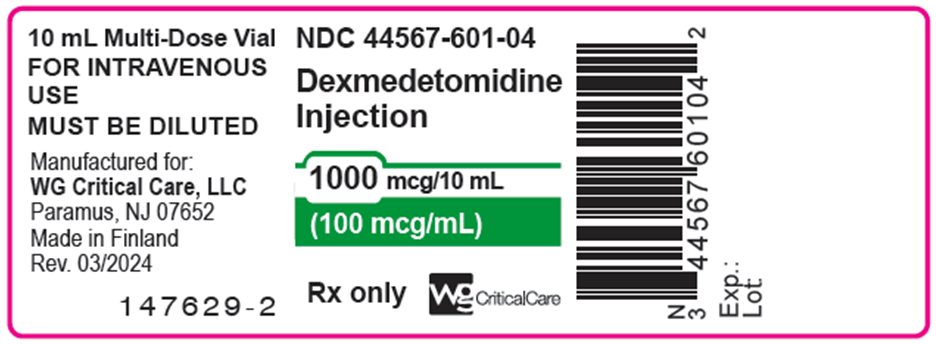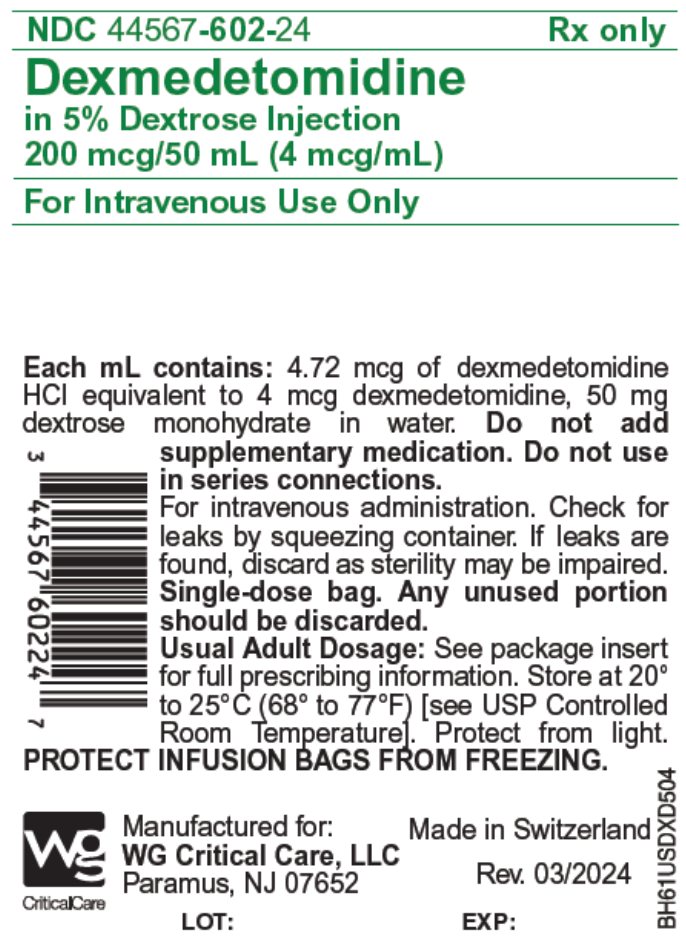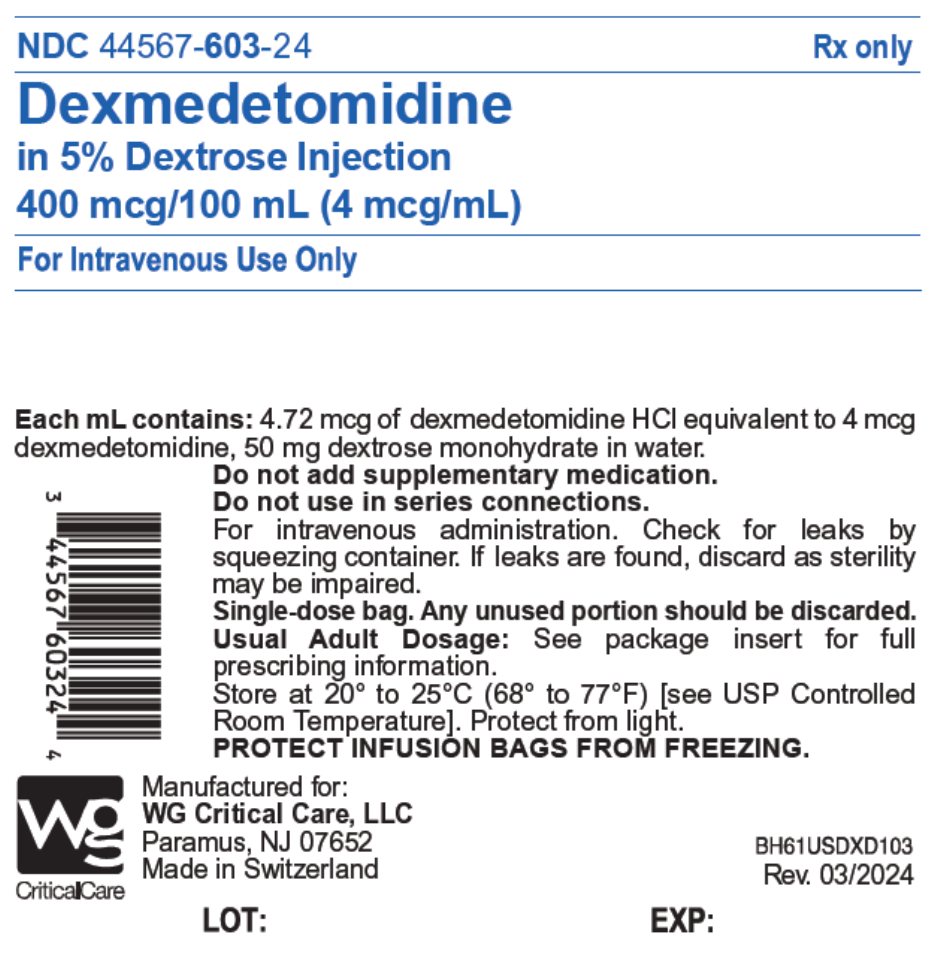 DRUG LABEL: Dexmedetomidine
NDC: 44567-600 | Form: INJECTION, SOLUTION, CONCENTRATE
Manufacturer: WG Critical Care, LLC
Category: prescription | Type: HUMAN PRESCRIPTION DRUG LABEL
Date: 20240331

ACTIVE INGREDIENTS: DEXMEDETOMIDINE HYDROCHLORIDE 100 ug/1 mL

HIGHLIGHTS OF PRESCRIBING INFORMATION

These highlights do not include all the information needed to use DEXMEDETOMIDINE INJECTION and DEXMEDETOMIDINE in DEXTROSE INJECTION safely and effectively. See full prescribing information for DEXMEDETOMIDINE INJECTION and DEXMEDETOMIDINE in DEXTROSE INJECTION.
DEXMEDETOMIDINE injection, for intravenous use
DEXMEDETOMIDINE in DEXTROSE injection, for intravenous use
Initial U.S. Approval: 1999

RECENT MAJOR CHANGES

Dosage and Administration (2.1, 2.3, 2.4, 2.5, 2.6) 03/2024

Warnings and Precautions (5) 03/2024

1 INDICATIONS AND USAGE

Dexmedetomidine Injection and Dexmedetomidine in 5% Dextrose Injection is a alpha2 adrenergic receptor agonist indicated for:

- Sedation of initially intubated and mechanically ventilated adult patients during treatment in an intensive care setting. Administer Dexmedetomidine Injection and Dexmedetomidine in 5% Dextrose Injection by continuous infusion not to exceed 24 hours. (1.1)
- Sedation of non-intubated adult patients prior to and/or during surgical and other procedures. (1.2)

2 DOSAGE AND ADMINISTRATION

- Individualize and titrate dosing to desired clinical effect. (2.1)
- Administration duration should not exceed 24 hours. (2.1)
- Administer intravenously using a controlled infusion device. (2.1)
- Dexmedetomidine Injection must be diluted prior to administration. (2.1)
- Dexmedetomidine Injection in 5% Dextrose 200 mcg/50 mL and 400 mcg/100 mL single-dose bags, do not require dilution prior to administration. (2.1)
- To be administered only by health care providers skilled in management of patients in the intensive care or operating room setting. (2.1)
- Continuously monitor blood pressure, heart rate, and oxygen levels during administration and as clinically appropriate after discontinuation. (2.1)
- It is not necessary to discontinue Dexmedetomidine Injection and Dexmedetomidine in 5% Dextrose Injection prior to extubation.
- For Adult Intensive Care Unit Sedation:
- Initiate at one mcg/kg over 10 minutes, followed by a maintenance infusion of 0.2 to 0.7 mcg/kg/hour. (2.2)
- For Adult Procedural Sedation: Initiate at one mcg/kg over 10 minutes, followed by a maintenance infusion initiated at 0.6 mcg/kg/hour and titrated to achieve desired clinical effect with doses ranging from 0.2 to 1 mcg/kg/hour. (2.2)
- Alternative Doses: Recommended for patients over 65 years of age and awake fiberoptic intubation patients. (2.2)
- See full prescribing information for recommended dosage, reconstitution, dilution, and administration instructions. (2.2, 2.3, 2.4 ,2.5, 2.6, 2.7)

3 DOSAGE FORMS AND STRENGTHS

Injection:

- 400 mcg/4 mL (100 mcg/mL) in a multiple-dose vial. (3)
- 1000 mcg/10 mL (100 mcg/mL) in a multiple-dose vial. (3)
- 200 mcg/50 mL (4 mcg/mL) in 5% Dextrose, single-dose, single-port flexible plastic ready-to-use infusion bag. (3)
- 400 mcg/100 mL (4 mcg/mL) in 5% Dextrose, single-dose, single-port flexible plastic ready-to-use infusion bag. (3)

4 CONTRAINDICATIONS

None. (4)

5 WARNINGS AND PRECAUTIONS

- Monitoring: Continuously monitor patients while receiving dexmedetomidine. (5.1)
- Bradycardia and Sinus Arrest: Have occurred in young healthy volunteers with high vagal tone or with different routes of administration, e.g., rapid intravenous or bolus administration. (5.2)
- Hypotension and Bradycardia: May necessitate medical intervention. May be more pronounced in patients with hypovolemia, diabetes mellitus, or chronic hypertension, and in the elderly. Use with caution in patients with advanced heart block or severe ventricular dysfunction. (5.2)
- Co-administration with Other Vasodilators or Negative Chronotropic Agents: Use with caution due to additive pharmacodynamic effects. (5.2)
- Transient Hypertension: Observed primarily during the loading dose. Consider reduction in loading infusion rate. (5.3)
- Arousability: Patients can become aroused/alert with stimulation; this alone should not be considered as lack of efficacy. (5.4)
- Tolerance and Tachyphylaxis: Prolonged exposure to dexmedetomidine beyond 24 hours may be associated with tolerance and tachyphylaxis and a dose-related increase in adverse events. (5.6)

6 ADVERSE REACTIONS

- The most common adverse reactions (incidence >2%) in adults are hypotension, bradycardia, and dry mouth. (6.1)
- Adverse reactions in adults, associated with infusions >24 hours in duration include ARDS, respiratory failure, and agitation. (6.1)

To report SUSPECTED ADVERSE REACTIONS, contact WG Critical Care at 1-866-562-4708 or FDA at 1-800-FDA-1088 or www.fda.gov/medwatch.

7 DRUG INTERACTIONS

Anesthetics, Sedatives, Hypnotics, Opioids: Enhancement of pharmacodynamic effects. Reduction in dosage of dexmedetomidine or the concomitant medication may be required. (7.1)

8 USE IN SPECIFIC POPULATIONS

- Geriatric Patients: Dose reduction should be considered. (2.2, 2.3, 5.2, 8.5)
- Hepatic Impairment: Dose reduction should be considered. (2.2, 2.3, 5.8, 8.6)

FULL PRESCRIBING INFORMATION

1 INDICATIONS AND USAGE

1.1 Intensive Care Unit Sedation

Dexmedetomidine Injection and Dexmedetomidine in 5% Dextrose Injectionis indicated for sedation of initially intubated and mechanically ventilated adult patients during treatment in an intensive care setting. Dexmedetomidine Injection and Dexmedetomidine in 5% Dextrose Injectionshould be administered by continuous infusion not to exceed 24 hours.

1.2 Procedural Sedation

Dexmedetomidine Injection and Dexmedetomidine in 5% Dextrose Injection is indicated for sedation of non-intubated adult patients prior to and/or during surgical and other procedures.

2 DOSAGE AND ADMINISTRATION

2.1 Administration Instructions

1. Individualize and titrate dosing to desired clinical response.
2. Administer by continuous intravenous infusion using a controlled infusion device.
3. Administration duration should not exceed 24 hours [see Warnings and Precautions (5.5, 5.6)].
4. Dexmedetomidine Injection must be diluted prior to administration [see Dosage and Administration (2.4)].
5. Dexmedetomidine in 5% Dextrose Injection 200 mcg/50 mL and 400mcg/100mL single-dose bags do not require further dilution prior to administration.
6. Dexmedetomidine Injection and Dexmedetomidine in 5% Dextrose Injectionshould be administered only by health care providers skilled in the management of patients in the intensive care or operating room setting.
7. Continuously monitor blood pressure, heart rate and oxygen levels during the use of Dexmedetomidine Injection and Dexmedetomidine in 5% Dextrose Injection and as clinically appropriate after discontinuation.
8. Dexmedetomidine Injection and Dexmedetomidine in 5% Dextrose Injectionhas been continuously infused in mechanically ventilated adult patients prior to extubation, during extubation, and post-extubation. It is not necessary to discontinue Dexmedetomidine Injection and Dexmedetomidine in 5% Dextrose Injectionprior to extubation.
9. Use administration components made with synthetic or coated natural rubber gaskets. Dexmedetomidine Injection and Dexmedetomidine in 5% Dextrose Injection has the potential for absorption into some types of natural rubber.

2.2 Recommended Dosage

Table 1: Recommended Dosage in Adult Patients
INDICATION | DOSAGE AND ADMINISTRATION
Initiation of Intensive Care Unit Sedation | For adult patients: a loading infusion of one mcg/kg over 10 minutes.; For adult patients being converted from alternate sedative therapy: a loading dose may not be required.; For patients over 65 years of age: Consider a dose reduction [see Use in Specific Populations (8.5)].; For adult patients with impaired hepatic function: Consider a dose reduction [see Use in Specific Populations (8.6), Clinical Pharmacology (12.3)].
Maintenance of Intensive Care Unit Sedation | For adult patients: a maintenance infusion of 0.2 to 0.7 mcg/kg/hour. The rate of the maintenance infusion should be adjusted to achieve the desired level of sedation.; For patients over 65 years of age: Consider a dose reduction [see Use in Specific Populations (8.5)].; For adult patients with impaired hepatic function: Consider a dose reduction [see Use in Specific Populations (8.6), Clinical Pharmacology (12.3)]
Initiation of Procedural Sedation | For adult patients: a loading infusion of one mcg/kg over 10 minutes. For less invasive procedures such as ophthalmic surgery, a loading infusion of 0.5 mcg/kg given over 10 minutes may be suitable.; For awake fiberoptic intubation in adult patients: a loading infusion of one mcg/kg over 10 minutes.; For patients over 65 years of age: a loading infusion of 0.5 mcg/kg over 10 minutes [see Use in Specific Populations (8.5)].; For adult patients with impaired hepatic function: Consider a dose reduction [see Use in Specific Populations (8.6), Clinical Pharmacology (12.3)].
Maintenance of Procedural Sedation | For adult patients: the maintenance infusion is generally initiated at 0.6 mcg/kg/hour and titrated to achieve desired clinical effect with doses ranging from 0.2 to 1 mcg/kg/hour. Adjust the rate of the maintenance infusion to achieve the targeted level of sedation.; For awake fiberoptic intubation in adult patients: a maintenance infusion of 0.7 mcg/kg/hour is recommended until the endotracheal tube is secured.; For patients over 65 years of age: Consider a dose reduction [see Use in Specific Populations (8.5)].; For adult patients with impaired hepatic function: Consider a dose reduction [see Use in Specific Populations (8.6), Clinical Pharmacology (12.3)].

2.3 Dosage Adjustment

Due to possible pharmacodynamic interactions, a reduction in dosage of dexmedetomidine or other concomitant anesthetics, sedatives, hypnotics or opioids may be required when co-administered [see Drug Interactions (7.1)]. Dosage reductions may need to be considered for adult patients with hepatic impairment, and geriatric patients [see Warnings and Precautions (5.8), Use in Specific Populations (8.6), Clinical Pharmacology (12.3)].

2.4 Preparation of Solution

Strict aseptic technique must always be maintained during handling of Dexmedetomidine Injection and Dexmedetomidine in 5% Dextrose Injection.

Parenteral drug products should be inspected visually for particulate matter and discoloration prior to

administration, whenever solution and container permit. Do not use if product is discolored or if precipitate matter is present.

Dexmedetomidine Injection, 400 mcg/4 mL (100 mcg/mL) and 1000 mcg/10 mL (100 mcg/mL)

Dexmedetomidine Injection must be diluted with 0.9% sodium chloride injection to achieve required concentration (4 mcg/mL) prior to administration. Preparation of solutions is the same, whether for the loading dose or maintenance infusion.

To prepare the solution, do one of the following:

- Withdraw 2 mL of Dexmedetomidine Injection, and add to 48 mL of 0.9% Sodium Chloride Injection to a total volume of 50 mL or
- Withdraw 4 mL of Dexmedetomidine Injection, and add to 96 mL of 0.9% Sodium Chloride Injection to a total of volume of 100 mL

Gently shake and mix well.

Prior to use, may store the diluted dexmedetomidine solution for up to 4 hours at room temperature or up to 24 hours at 2o to 8oC.

Discard unused portion.

Dexmedetomidine in 5% Dextrose Injection,200 mcg/50 mL (4 mcg/mL) and 400 mcg/100 mL (4 mcg/mL)

Dexmedetomidine in 5% Dextrose Injectionis supplied in single-port, flexible plastic ready-to-use infusion bags with dexmedetomidine solution in 5% dextrose in water. No further dilution of these preparations is necessary.

2.5 Administration with Other Fluids

Dexmedetomidine Injection and Dexmedetomidine in 5% Dextrose Injection should not be co-administered through the same intravenous catheter with blood or plasma because physical compatibility has not been established. Dexmedetomidine Injection and Dexmedetomidine in 5% Dextrose Injection has been shown to be incompatible when administered with the following drugs: amphotericin B, diazepam.

Dexmedetomidine Injection and Dexmedetomidine in 5% Dextrose Injection is compatible with and may be co-administered with:

- 0.9% Sodium Chloride Injection
- 5% Dextrose Injection in water
- 20% Mannitol Injection
- Lactated Ringer’s Injection
- 100 mg/mL Magnesium Sulfate Injection
- 0.3% potassium chloride solution

2.6 Compatibility with Natural Rubber

Compatibility studies have demonstrated the potential for absorption of dexmedetomidine to some types of natural rubber. Although dexmedetomidine is dosed to effect, it is advisable to use administration components made with synthetic or coated natural rubber gaskets.

3 DOSAGE FORMS AND STRENGTHS

Dexmedetomidine Injection is clear, colorless, sterile, and nonpyrogenic solution suitable for intravenous infusion following dilution and is available in 100 mcg/mL strength as follows:

- 400 mcg/4 mL (100 mcg/mL) in a multiple-dose vial
- 1000 mcg in 10 mL in a multiple-dose vial

Dexmedetomidine in 5% Dextrose Injection is clear, colorless, sterile ready-to-use, and nonpyrogenic solution suitable for intravenous infusion and is available in 4 mcg/mL strength as follows:

- 200 mcg/50 mL single-dose, single-port flexible plastic infusion bag
- 400 mcg/100 mL single-dose, single-port flexible plastic infusion bag

4 CONTRAINDICATIONS

None.

5 WARNINGS AND PRECAUTIONS

5.1 Drug Administration

Dexmedetomidine should be administered only by persons skilled in the management of patients in the intensive care or operating room setting. Due to the known pharmacological effects of dexmedetomidine, patients should be continuously monitored while receiving dexmedetomidine.

5.2 Hypotension, Bradycardia and Sinus Arrest

Clinically significant episodes of bradycardia and sinus arrest have been reported with dexmedetomidine administration in young, healthy adult volunteers with high vagal tone or with different routes of administration including rapid intravenous or bolus administration.

Reports of hypotension and bradycardia have been associated with dexmedetomidine infusion. Some of these cases have resulted in fatalities. If medical intervention is required, treatment may include decreasing or stopping the infusion of dexmedetomidine, increasing the rate of intravenous fluid administration, elevation of the lower extremities, and use of pressor agents. Because dexmedetomidine has the potential to augment bradycardia induced by vagal stimuli, clinicians should be prepared to intervene. The intravenous administration of anticholinergic agents (e.g., glycopyrrolate, atropine) should be considered to modify vagal tone. In clinical trials, glycopyrrolate or atropine were effective in the treatment of most episodes of dexmedetomidine-induced bradycardia. However, in some patients with significant cardiovascular dysfunction, more advanced resuscitative measures were required.

Caution should be exercised when administering dexmedetomidine to patients with advanced heart block and/or severe ventricular dysfunction. Because dexmedetomidine decreases sympathetic nervous system activity, hypotension and/or bradycardia may be expected to be more pronounced in patients with hypovolemia, diabetes mellitus, or chronic hypertension and in elderly patients.

In clinical trials where other vasodilators or negative chronotropic agents were co-administered with dexmedetomidine an additive pharmacodynamic effect was not observed. Nonetheless, caution should be used when such agents are administered concomitantly with dexmedetomidine.

5.3 Transient Hypertension

Transient hypertension has been observed primarily during the loading dose in association with the initial peripheral vasoconstrictive effects of dexmedetomidine. Treatment of the transient hypertension has generally not been necessary, although reduction of the loading infusion rate may be desirable.

5.4 Arousability

Some patients receiving dexmedetomidine have been observed to be arousable and alert when stimulated. This alone should not be considered as evidence of lack of efficacy in the absence of other clinical signs and symptoms.

5.5 Withdrawal

Intensive Care Unit Sedation

With administration up to 7 days, regardless of dose, 12 (5%) dexmedetomidine adult subjects experienced at least 1 event related to withdrawal within the first 24 hours after discontinuing study drug and 7 (3%) dexmedetomidine adult subjects experienced at least 1 event 24 to 48 hours after end of study drug. The most common events were nausea, vomiting, and agitation [see Adverse Reactions (6.1)].

In adult subjects, tachycardia and hypertension requiring intervention in the 48 hours following study drug discontinuation occurred at frequencies of <5%.

Procedural Sedation

In adult subjects, withdrawal symptoms were not seen after discontinuation of short-term infusions of dexmedetomidine (<6 hours).

In pediatric patients, mild transient withdrawal symptoms of emergence delirium or agitation were seen after discontinuation of short-term infusions of dexmedetomidine (<2 hours).

5.6 Tolerance and Tachyphylaxis

Use of dexmedetomidine beyond 24 hours has been associated with tolerance and tachyphylaxis and a dose-related increase in adverse reactions. [see Adverse Reactions (6.1)].

5.7 Hyperthermia or Pyrexia

Dexmedetomidine may induce hyperthermia or pyrexia, which may be resistant to traditional cooling methods, such as administration of cooled intravenous fluids and antipyretic medications. Discontinue dexmedetomidine if drug-related hyperthermia or pyrexia is suspected and monitor patients until body temperature normalizes.

5.8 Hepatic Impairment

Since dexmedetomidine clearance decreases with severity of hepatic impairment, dose reduction should be considered in patients with impaired hepatic function [see Dosage and Administration (2.2, 2.3)].

6 ADVERSE REACTIONS

The following clinically significant adverse reactions are described elsewhere in the labeling:

- Hypotension, bradycardia and sinus arrest [see Warnings and Precautions (5.2)]
- Transient hypertension [see Warnings and Precautions (5.3)]

6.1 Clinical Trials Experience

Because clinical trials are conducted under widely varying conditions, adverse reactions rates observed in the clinical trials of a drug cannot be directly compared to rates in the clinical trials of another drug and may not reflect the rates observed in practice.

Most common treatment-emergent adverse reactions, occurring in greater than 2% of adult patients in both Intensive Care Unit and procedural sedation studies include hypotension, bradycardia and dry mouth.

Intensive Care Unit Sedation

Adverse reaction information is derived from the continuous infusion trials of dexmedetomidine for sedation in the Intensive Care Unit setting in which 1,007 adult patients received dexmedetomidine. The mean total dose was 7.4 mcg/kg (range: 0.8 to 84.1), mean dose per hour was 0.5 mcg/kg/hr (range: 0.1 to 6.0) and the mean duration of infusion of 15.9 hours (range: 0.2 to 157.2). The population was between 17 to 88 years of age, 43% ≥65 years of age, 77% male and 93% Caucasian. Treatment-emergent adverse reactions occurring at an incidence of >2% are provided in Table 2. The most frequent adverse reactions were hypotension, bradycardia and dry mouth [see Warnings and Precautions (5.2)].

Table 2: Adverse Reactions with an Incidence >2%— Adult Intensive Care Unit Sedation Population <24 hours*

Adverse Event | All Dexmedetomidine (N = 1007) (%) | Randomized Dexmedetomidine (N = 798) (%) | Placebo (N = 400) (%) | Propofol (N = 188) (%)
Hypotension | 25% | 24% | 12% | 13%
Hypertension | 12% | 13% | 19% | 4%
Nausea | 9% | 9% | 9% | 11%
Bradycardia | 5% | 5% | 3% | 0
Atrial Fibrillation | 4% | 5% | 3% | 7%
Pyrexia | 4% | 4% | 4% | 4%
Dry Mouth | 4% | 3% | 1% | 1%
Vomiting | 3% | 3% | 5% | 3%
Hypovolemia | 3% | 3% | 2% | 5%
Atelectasis | 3% | 3% | 3% | 6%
Pleural Effusion | 2% | 2% | 1% | 6%
Agitation | 2% | 2% | 3% | 1%
Tachycardia | 2% | 2% | 4% | 1%
Anemia | 2% | 2% | 2% | 2%
Hyperthermia | 2% | 2% | 3% | 0
Chills | 2% | 2% | 3% | 2%
Hyperglycemia | 2% | 2% | 2% | 3%
Hypoxia | 2% | 2% | 2% | 3%
Post-procedural Hemorrhage | 2% | 2% | 3% | 4%
Pulmonary Edema | 1% | 1% | 1% | 3%
Hypocalcemia | 1% | 1% | 0 | 2%
Acidosis | 1% | 1% | 1% | 2%
Urine Output Decreased | 1% | 1% | 0 | 2%
Sinus Tachycardia | 1% | 1% | 1% | 2%
Ventricular Tachycardia | <1% | 1% | 1% | 5%
Wheezing | <1% | 1% | 0 | 2%
Edema Peripheral | <1% | 0 | 1% | 2%
*26 subjects in the all dexmedetomidine group and 10 subjects in the randomized dexmedetomidine group had exposure for greater than 24 hours.

Adverse reaction information was also derived from the placebo-controlled, continuous infusion trials of dexmedetomidine for sedation in the surgical intensive care unit setting in which 387 adult patients received dexmedetomidine for less than 24 hours. The most frequently observed treatment-emergent adverse events included hypotension, hypertension, nausea, bradycardia, fever, vomiting, hypoxia, tachycardia and anemia (see Table 3).

Table 3: Treatment-Emergent Adverse Events Occurring in >1% of All Dexmedetomidine-Treated Adult Patients in the Randomized Placebo-Controlled Continuous Infusion <24 Hours ICU Sedation Studies

Adverse Event | Randomized Dexmedetomidine (N = 387) | Placebo (N = 379)
Hypotension | 28% | 13%
Hypertension | 16% | 18%
Nausea | 11% | 9%
Bradycardia | 7% | 3%
Fever | 5% | 4%
Vomiting | 4% | 6%
Atrial Fibrillation | 4% | 3%
Hypoxia | 4% | 4%
Tachycardia | 3% | 5%
Hemorrhage | 3% | 4%
Anemia | 3% | 2%
Dry Mouth | 3% | 1%
Rigors | 2% | 3%
Agitation | 2% | 3%
Hyperpyrexia | 2% | 3%
Pain | 2% | 2%
Hyperglycemia | 2% | 2%
Acidosis | 2% | 2%
Pleural Effusion | 2% | 1%
Oliguria | 2% | <1%
Thirst | 2% | <1%

In a controlled clinical trial, dexmedetomidine was compared to midazolam for ICU sedation exceeding 24 hours duration in adult patients. Key treatment emergent adverse events occurring in dexmedetomidine or midazolam treated adult patients in the randomized active comparator continuous infusion long-term intensive care unit sedation study are provided in Table 4. The number (%) of adult subjects who had a dose-related increase in treatment-emergent adverse events by maintenance adjusted dose rate range in the dexmedetomidine group is provided in Table 5.

Table 4: Key Treatment-Emergent Adverse Events Occurring in Dexmedetomidine- or Midazolam-Treated Adult Patients in the Randomized Active Comparator Continuous Infusion Long-Term Intensive Care Unit Sedation Study

Adverse Event | Dexmedetomidine (N = 244) | Midazolam (N = 122)
Hypotension^1 | 56% | 56%
Hypotension Requiring Intervention | 28% | 27%
Bradycardia^2 | 42% | 19%
Bradycardia Requiring Intervention | 5% | 1%
Systolic Hypertension^3 | 28% | 42%
Tachycardia^4 | 25% | 44%
Tachycardia Requiring Intervention | 10% | 10%
Diastolic Hypertension^3 | 12% | 15%
Hypertension^3 | 11% | 15%
Hypertension Requiring Intervention† | 19% | 30%
Hypokalemia | 9% | 13%
Pyrexia | 7% | 2%
Agitation | 7% | 6%
Hyperglycemia | 7% | 2%
Constipation | 6% | 6%
Hypoglycemia | 5% | 6%
Respiratory Failure | 5% | 3%
Renal Failure Acute | 2% | 1%
Acute Respiratory Distress Syndrome | 2% | 1%
Generalized Edema | 2% | 6%
Hypomagnesemia | 1% | 7%
† Includes any type of hypertension.
^1 Hypotension was defined in absolute terms as Systolic blood pressure of <80 mmHg or Diastolic blood pressure of <50 mmHg or in relative terms as ≤30% lower than pre-study drug infusion value.
^2 Bradycardia was defined in absolute terms as <40 bpm or in relative terms as ≤30% lower than pre-study drug infusion value.
^3 Hypertension was defined in absolute terms as Systolic blood pressure >180 mmHg or Diastolic blood pressure of >100 mmHg or in relative terms as ≥30% higher than pre-study drug infusion value.
^4 Tachycardia was defined in absolute terms as >120 bpm or in relative terms as ≥30% greater than pre-study drug infusion value.

The following adverse events occurred between 2 and 5% for dexmedetomidine and Midazolam, respectively: renal failure acute (2.5%, 0.8%), acute respiratory distress syndrome (2.5%, 0.8%), and respiratory failure (4.5%, 3.3%).

Table 5. Number (%) of Adult Subjects Who Had a Dose-Related Increase in Treatment Emergent Adverse Events by Maintenance Adjusted Dose Rate Range in the Dexmedetomidine Group

Dexmedetomidine mcg/kg/hr
Adverse Event | ≤0.7* (N = 95) | >0.7 to ≤1.1* (N = 78) | >1.1* (N = 71)
Constipation | 6% | 5% | 14%
Agitation | 5% | 8% | 14%
Anxiety | 5% | 5% | 9%
Edema Peripheral | 3% | 5% | 7%
Atrial Fibrillation | 2% | 4% | 9%
Respiratory Failure | 2% | 6% | 10%
Acute Respiratory Distress Syndrome | 1% | 3% | 9%
*Average maintenance dose over the entire study drug administration

Adult Procedural Sedation

Adverse reaction information is derived from the two trials for adult procedural sedation [see Clinical Studies (14.2)] in which 318 adult patients received dexmedetomidine. The mean total dose was 1.6 mcg/kg (range: 0.5 to 6.7), mean dose per hour was 1.3 mcg/kg/hr (range: 0.3 to 6.1) and the mean duration of infusion of 1.5 hours (range: 0.1 to 6.2). The population was between 18 to 93 years of age, ASA I-IV, 30% ≥ 65 years of age, 52% male and 61% Caucasian.

Treatment-emergent adverse reactions occurring in adults at an incidence of >2% are provided in Table 6. The most frequent adverse reactions were hypotension, bradycardia, and dry mouth [see Warnings and Precautions (5.2)]. Pre-specified criteria for the vital signs to be reported as adverse reactions are footnoted below the table. The decrease in respiratory rate and hypoxia was similar between dexmedetomidine and comparator groups in both studies.

Table 6: Adverse Reactions that Occurred with an Incidence of Greater than 2% and Greater in the Placebo Group in Clinical Trials of Dexmedetomidine for Adult Procedural

Adverse Event | Dexmedetomidine (N = 318) (%) | Placebo (N = 113) (%)
Hypotension^1 | 54% | 30%
Respiratory Depression^2 | 37% | 32%
Bradycardia^3 | 14% | 4%
Hypertension^4 | 13% | 24%
Tachycardia^5 | 5% | 17%
Nausea | 3% | 2%
Dry Mouth | 3% | 1%
Hypoxia^6 | 2% | 3%
Bradypnea | 2% | 4%
^1 Hypotension was defined in absolute and relative terms as Systolic blood pressure of <80 mmHg or ≤30% lower than pre-study drug infusion value, or Diastolic blood pressure of <50 mmHg.
^2 Respiratory depression was defined in absolute and relative terms as respiratory rate (RR) <8 beats per minute or >25% decrease from baseline.
^3 Bradycardia was defined in absolute and relative terms as <40 beats per minute or ≤30% lower than pre-study drug infusion value. Subjects in Study 2 were pretreated with glycopyrrolate 0.1 mg intravenously before receiving study drug [see Clinical Studies (14.2)].
^4 Hypertension was defined in absolute and relative terms as Systolic blood pressure >180 mmHg or ≥30% higher than pre-study drug infusion value or Diastolic blood pressure of >100 mmHg.
^5 Tachycardia was defined in absolute and relative terms as >120 beats per minute or ≥30% greater than pre-study drug infusion value.
^6 Hypoxia was defined in absolute and relative terms as SpO2 <90% or 10% decrease from baseline.

6.2 Postmarketing Experience

The following adverse reactions have been identified during post-approval use of dexmedetomidine. Because these reactions are reported voluntarily from a population of uncertain size, it is not always possible to reliably estimate their frequency or establish a causal relationship to drug exposure.

Hypotension and bradycardia were the most common adverse reactions associated with the use of dexmedetomidine during post approval use of the drug.

Table 7: Adverse Reactions Experienced During Post-Approval Use of Dexmedetomidine
System Organ Class | Preferred Term
Blood and Lymphatic System Disorders | Anemia
Cardiac Disorders | Arrhythmia, atrial fibrillation, atrioventricular block, bradycardia, cardiac arrest, cardiac disorder, extrasystoles, myocardial infarction, supraventricular tachycardia, tachycardia, ventricular arrhythmia, ventricular tachycardia
Eye Disorders | Photopsia, visual impairment
Gastrointestinal Disorders | Abdominal pain, diarrhea, nausea, vomiting
General Disorders and Administration Site Conditions | Chills, hyperpyrexia, pain, pyrexia, thirst
Hepatobiliary Disorders | Hepatic function abnormal, hyperbilirubinemia
Investigations | Alanine aminotransferase increased, aspartate aminotransferase increased, blood alkaline phosphatase increased, blood urea increased, electrocardiogram T wave inversion, gammaglutamyltransferase increased, electrocardiogram QT prolonged
Metabolism and Nutrition Disorders | Acidosis, hyperkalemia, hypoglycemia, hypovolemia, hypernatremia
Nervous System Disorders | Convulsion, dizziness, headache, neuralgia, neuritis, speech disorder
Psychiatric Disorders | Agitation, confusional state, delirium, hallucination, illusion
Renal and Urinary Disorders | Oliguria, polyuria
Respiratory, Thoracic and Mediastinal Disorders | Apnea, bronchospasm, dyspnea, hypercapnia, hypoventilation, hypoxia, pulmonary congestion, respiratory acidosis
Skin and Subcutaneous Tissue Disorders | Hyperhidrosis, pruritus, rash, urticaria
Surgical and Medical Procedures | Light anesthesia
Vascular Disorders | Blood pressure fluctuation, hemorrhage, hypertension, hypotension

7 DRUG INTERACTIONS

7.1 Anesthetics, Sedatives, Hypnotics, Opioids

Co-administration of dexmedetomidine with anesthetics, sedatives, hypnotics, and opioids is likely to lead to an enhancement of effects. Specific studies have confirmed these effects with sevoflurane, isoflurane, propofol, alfentanil, and midazolam. No pharmacokinetic interactions between dexmedetomidine and isoflurane, propofol, alfentanil and midazolam have been demonstrated. However, due to possible pharmacodynamic interactions, when co-administered with dexmedetomidine, a reduction in dosage of dexmedetomidine or the concomitant anesthetic, sedative, hypnotic or opioid may be required.

7.2 Neuromuscular Blockers

In one study of 10 healthy adult volunteers, administration of dexmedetomidine for 45 minutes at a plasma concentration of one ng/mL resulted in no clinically meaningful increases in the magnitude of neuromuscular blockade associated with rocuronium administration.

8 USE IN SPECIFIC POPULATIONS

8.1 Pregnancy

Risk Summary

Available data from published randomized controlled trials and case reports over several decades of use with intravenously administered dexmedetomidine during pregnancy have not identified a drug-associated risk of major birth defects and miscarriage; however, the reported exposures occurred after the first trimester. Most of the available data are based on studies with exposures that occurred at the time of caesarean section delivery, and these studies have not identified an adverse effect on maternal outcomes or infant Apgar scores. Available data indicate that dexmedetomidine crosses the placenta.

In animal reproduction studies, fetal toxicity that lower fetal viability and reduced live fetuses occurred with subcutaneous administration of dexmedetomidine to pregnant rats during organogenesis at doses 1.8 times the maximum recommended human dose (MRHD) of 17.8 mcg/kg/day.

Developmental toxicity (low pup weights and adult offspring weights, decreased F1 grip strength, increased early implantation loss and decreased viability of second-generation offspring) occurred when pregnant rats were subcutaneously administered dexmedetomidine at doses less than the clinical dose from late pregnancy through lactation and weaning (see Data).

The estimated background risk of major birth defects and miscarriage for the indicated population is unknown. All pregnancies have a background risk of birth defect, loss, or other adverse outcomes. In the U.S. general population, the estimated background risk of major birth defects and miscarriage in clinically recognized pregnancies is 2-4% and 15-20%, respectively.

Data

Animal Data

Increased post-implantation losses and reduced live fetuses in the presence of maternal toxicity (i.e. decreased body weight) were noted in a rat embryo-fetal development study in which pregnant dams were administered subcutaneous doses of dexmedetomidine 200 mcg/kg/day (equivalent to 1.8 times the intravenous MRHD of 17.8 mcg/kg/day based on body surface area [BSA]) during the period of organogenesis (Gestation Day [GD] 6 to 15). No malformations were reported.

No malformations or embryo-fetal toxicity were noted in a rabbit embryo-fetal development study in which pregnant does were administered dexmedetomidine intravenously at doses of up to 96 mcg/kg/day (approximately half the human exposure at the MRHD based on AUC) during the period of organogenesis (GD 6 to 18).

Reduced pup and adult offspring birth weights, and grip strength were reported in a rat developmental toxicology study in which pregnant females were administered dexmedetomidine subcutaneously at doses of 8 mcg/kg/day (0.07 times the MRHD based on BSA) during late pregnancy through lactation and weaning (GD 16 to postnatal day [PND] 25). Decreased viability of second generation offspring and an increase in early implantation loss along with delayed motor development occurred in the 32 mcg/kg/day group (equivalent to less than the clinical dose based on BSA) when first generation offspring were allowed to mate. This study limited dosing to hard palate closure (GD 15 to 18) through weaning instead of dosing from implantation (GD 6 to 7) to weaning (PND 21).

In a study in the pregnant rat, placental transfer of dexmedetomidine was observed when radiolabeled dexmedetomidine was administered subcutaneously.

8.2 Lactation

Risk Summary

Available published literature reports the presence of dexmedetomidine in human milk following intravenous administration (see Data). There is no information regarding the effects of dexmedetomidine on the breastfed infant or the effects on milk production. Advise women to monitor the breastfed infant for irritability. The developmental and health benefits of breastfeeding should be considered along with the mother’s clinical need for dexmedetomidine and any potential adverse effects on the breastfed infant from dexmedetomidine or from the underlying condition.

Data

In two published clinical studies, a total of 14 women were given intravenous dexmedetomidine 6 mcg/kg/hour for 10 minutes after delivery followed by continuous infusion of 0.2–0.7 mcg/kg/hour. Breast milk and maternal blood samples were collected at 0, 6, 12, and 24 hours after discontinuation of dexmedetomidine. Plasma and milk dexmedetomidine concentrations were detectable up to 6 hours in most subjects, up to 12 hours in one subject and undetectable in all at 24 hours. The milk-to-plasma ratio from single paired maternal milk and plasma concentrations at each time point ranged from 0.53 to 0.95. The relative infant dose was estimated to range from 0.02 to 0.098%.

8.4 Pediatric Use

Safety and efficacy of dexmedetomidine have not been established for Procedural or ICU Sedation in pediatric patients.

8.5 Geriatric Use

Intensive Care Unit Sedation

A total of 729 patients in the clinical studies were 65 years of age and over. A total of 200 patients were 75 years of age and over. In patients greater than 65 years of age, a higher incidence of bradycardia and hypotension was observed following administration of dexmedetomidine [see Warnings and Precautions (5.1, 5.2)]. Therefore a dose reduction may be considered in patients over 65 years of age [see Dosage and Administration (2.3) and Clinical Pharmacology (12.3)].

Procedural Sedation

A total of 131 patients in the clinical studies were 65 years of age and over. A total of 47 patients were 75 years of age and over. Hypotension occurred in a higher incidence in dexmedetomidine-treated patients 65 years or older (72%) and 75 years or older (74%) as compared to patients <65 years (47%). A reduced loading dose of 0.5 mcg/kg given over 10 minutes is recommended and a reduction in the maintenance infusion should be considered for patients greater than 65 years of age.

8.6 Hepatic Impairment

Since dexmedetomidine clearance decreases with increasing severity of hepatic impairment, dose reduction should be considered in patients with impaired hepatic function [see Dosage and Administration (2.2, 2.3), Clinical Pharmacology (12.3)].

9 DRUG ABUSE AND DEPENDENCE

9.1 Controlled Substance

Dexmedetomidine is not a controlled substance

9.3 Dependence

The dependence potential of dexmedetomidine has not been studied in humans. However, since studies in rodents and primates have demonstrated that dexmedetomidine exhibits pharmacologic actions similar to those of clonidine, it is possible that dexmedetomidine may produce a clonidine-like withdrawal syndrome upon abrupt discontinuation [see Warnings and Precautions (5.5)].

10 OVERDOSAGE

The tolerability of dexmedetomidine was studied in one study in which healthy adult subjects were administered doses at and above the recommended dose of 0.2 to 0.7 mcg/kg/hr. The maximum blood concentration achieved in this study was approximately 13 times the upper boundary of the therapeutic range. The most notable effects observed in two subjects who achieved the highest doses were first degree atrioventricular block and second-degree heart block. No hemodynamic compromise was noted with the atrioventricular block and the heart block resolved spontaneously within one minute.

Five adult patients received an overdose of dexmedetomidine in the intensive care unit sedation studies. Two of these patients had no symptoms reported; one patient received a 2 mcg/kg loading dose over 10 minutes (twice the recommended loading dose) and one patient received a maintenance infusion of 0.8 mcg/kg/hr. Two other patients who received a 2 mcg/kg loading dose over 10 minutes, experienced bradycardia and/or hypotension. One patient who received a loading bolus dose of undiluted dexmedetomidine (19.4 mcg/kg), had cardiac arrest from which he was successfully resuscitated.

11 DESCRIPTION

Dexmedetomidine Injection is a sterile, nonpyrogenic solution suitable for intravenous infusion following dilution. Dexmedetomidine in 5% Dextrose Injection is a sterile ready-to-use, nonpyrogenic solution suitable for intravenous infusion. Dexmedetomidine Injection and Dexmedetomidine in Dextrose Injection contains the dexmedetomidine as active pharmaceutical ingredient in the form of the hydrochloride salt form.

Dexmedetomidine hydrochloride is a central alpha-2 adrenergic agonist. Structurally it is the S-enantiomer of medetomidine and is chemically described as 4-[(S)-α,2,3-Trimethylbenzyl]imidazole monohydrochloride. Dexmedetomidine hydrochloride has a molecular weight of 236.74 and the empirical formula is C13H16N2 • HCl and the structural formula is:

Dexmedetomidine hydrochloride is a white or almost white powder that is freely soluble in water and has a pKa of 7.1. Its partition coefficient in-octanol: water at pH 7.4 is 2.89.

Dexmedetomidine Injection is supplied as a clear, colorless, isotonic solution with a pH of 4.5 to 7. Each mL contains 118 mcg of dexmedetomidine hydrochloride USP, equivalent to 100 mcg (0.1 mg) of dexmedetomidine, 1.6 mg of methylparaben NF and 0.2 mg of propylparaben NF, as preservatives and 9 mg of sodium chloride USP, as tonicity agent in water for injection.

Dexmedetomidine in 5% Dextrose Injection is supplied as a clear, colorless, isotonic solution with a pH of 4.5 to 7. Each mL contains 4.72 mcg of dexmedetomidine hydrochloride USP, equivalent to 4 mcg of dexmedetomidine, and 50 mg dextrose monohydrate USP, as tonicity agent, in water for injection.

12 CLINICAL PHARMACOLOGY

12.1 Mechanism of Action

Dexmedetomidine is a relatively selective centrally acting alpha2-adrenergic agonist with sedative properties. Alpha2 selectivity was observed in animals following slow intravenous infusion of low and medium doses (10 mcg/kg to 300 mcg/kg). Both alpha1 and alpha2 activity is observed following slow intravenous infusion of high doses (greater than or equal to 1000 mcg/kg) or with rapid intravenous administration.

12.2 Pharmacodynamics

In a study in healthy adult volunteers (N = 10), respiratory rate and oxygen saturation remained within normal limits and there was no evidence of respiratory depression when dexmedetomidine was administered by intravenous infusion at doses within the recommended dose range (0.2–0.7 mcg/kg/hr).

12.3 Pharmacokinetics

Following intravenous administration to adults, dexmedetomidine exhibits the following pharmacokinetic parameters: a rapid distribution phase with a distribution half-life (t1/2) of approximately 6 minutes; a terminal elimination half-life (t1/2) of approximately 2 hours; and steady-state volume of distribution (Vss) of approximately 118 liters. Clearance is estimated to be approximately 39 L/hour. The mean body weight associated with this clearance estimate was 72 kg.

Dexmedetomidine exhibits linear pharmacokinetics in the dosage range of 0.2 to 0.7 mcg/kg/hr when administered to adults by intravenous infusion for up to 24 hours. Table 8 shows the main pharmacokinetic parameters when dexmedetomidine was infused (after appropriate loading doses) at maintenance infusion rates of 0.17 mcg/kg/hr (target plasma concentration of 0.3 ng/mL) for 12 and 24 hours, 0.33 mcg/kg/hr (target plasma concentration of 0.6 ng/mL) for 24 hours, and 0.70 mcg/kg/hr (target plasma concentration of 1.25 ng/mL) for 24 hours.

Table 8: Mean ± SD Pharmacokinetic Parameters in Adults

Parameter | Loading Infusion (min)/Total Infusion Duration (hrs)
Parameter | 10 min/12 hrs | 10 min/24 hrs | 10 min/24 hrs | 35 min/24 hrs
Parameter | Dexmedetomidine Target Plasma Concentration (ng/mL) and Dose (mcg/kg/hr)
Parameter | 0.3/0.17 | 0.3/0.17 | 0.6/0.33 | 1.25/0.70
t1/2*, hour | 1.78 ± 0.30 | 2.22 ± 0.59 | 2.23 ± 0.21 | 2.50 ± 0.61
CL, liter/hour | 46.3 ± 8.3 | 43.1 ± 6.5 | 35.3 ± 6.8 | 36.5 ± 7.5
Vss, liter | 88.7 ± 22.9 | 102.4 ± 20.3 | 93.6 ± 17.0 | 99.6 ± 17.8
Avg Css #, ng/mL | 0.27 ± 0.05 | 0.27 ± 0.05 | 0.67 ± 0.10 | 1.37 ± 0.20
Abbreviations: t1/2 = half-life, CL = clearance, Vss = steady-state volume of distribution.
* Presented as harmonic mean and pseudo standard deviation.
# Mean Css = Average steady-state concentration of dexmedetomidine. The mean Css was calculated based on post-dose sampling from 2.5 to 9 hours samples for 12 hour infusion and post-dose sampling from 2.5 to 18 hours for 24 hour infusions.
The loading doses for each of the above indicated groups were 0.5, 0.5, 1 and 2.2 mcg/kg, respectively.

Dexmedetomidine pharmacokinetic parameters in adults after dexmedetomidine maintenance doses of 0.2 to 1.4 mcg/kg/hr for >24 hours were similar to the pharmacokinetics (PK) parameters after dexmedetomidine maintenance dosing for < 24 hours in other studies. The values for clearance (CL), volume of distribution (V), and t1/2 were 39.4 L/hr, 152 L, and 2.67 hours, respectively.

Distribution

The steady-state volume of distribution (Vss) of dexmedetomidine was approximately 118 liters. Dexmedetomidine protein binding was assessed in the plasma of normal healthy male and female subjects. The average protein binding was 94% and was constant across the different plasma concentrations tested. Protein binding was similar in males and females. The fraction of dexmedetomidine that was bound to plasma proteins was significantly decreased in subjects with hepatic impairment compared to healthy subjects.

The potential for protein binding displacement of dexmedetomidine by fentanyl, ketorolac, theophylline, digoxin and lidocaine was explored in vitro, and negligible changes in the plasma protein binding of dexmedetomidine were observed. The potential for protein binding displacement of phenytoin, warfarin, ibuprofen, propranolol, theophylline and digoxin by dexmedetomidine was explored in vitro and none of these compounds appeared to be significantly displaced by dexmedetomidine.

Elimination

Metabolism

Dexmedetomidine undergoes almost complete biotransformation with very little unchanged dexmedetomidine excreted in urine and feces. Biotransformation involves both direct glucuronidation as well as cytochrome P450 mediated metabolism. The major metabolic pathways of dexmedetomidine are: direct N-glucuronidation to inactive metabolites; aliphatic hydroxylation (mediated primarily by CYP2A6 with a minor role of CYP1A2, CYP2E1, CYP2D6 and CYP2C19) of dexmedetomidine to generate 3-hydroxy-dexmedetomidine, the glucuronide of 3-hydroxy-dexmedetomidine, and 3-carboxy-dexmedetomidine; and N-methylation of dexmedetomidine to generate 3-hydroxy N-methyl-dexmedetomidine, 3-carboxy N-methyl-dexmedetomidine, and dexmedetomidine-N-methyl O-glucuronide.

Excretion

The terminal elimination half-life (t1/2) of dexmedetomidine is approximately 2 hours and clearance is estimated to be approximately 39 L/h. A mass balance study demonstrated that after nine days an average of 95% of the radioactivity, following intravenous administration of radiolabeled dexmedetomidine, was recovered in the urine and 4% in the feces. No unchanged dexmedetomidine was detected in the urine. Approximately 85% of the radioactivity recovered in the urine was excreted within 24 hours after the infusion. Fractionation of the radioactivity excreted in urine demonstrated that products of N-glucuronidation accounted for approximately 34% of the cumulative urinary excretion. In addition, aliphatic hydroxylation of parent drug to form 3-hydroxy-dexmedetomidine, the glucuronide of 3-hydroxy-dexmedetomidine, and 3-carboxylic acid-dexmedetomidine together represented approximately 14% of the dose in urine. N-methylation of dexmedetomidine to form 3-hydroxy N-methyl dexmedetomidine, 3-carboxy N-methyl dexmedetomidine, and N-methyl O-glucuronide dexmedetomidine accounted for approximately 18% of the dose in urine. The N-Methyl metabolite itself was a minor circulating component and was undetected in urine. Approximately 28% of the urinary metabolites have not been identified.

Specific Populations

Male and Female Patients

There was no observed difference in dexmedetomidine pharmacokinetics due to sex.

Geriatric Patients

The pharmacokinetic profile of dexmedetomidine was not altered by age. There were no differences in the pharmacokinetics of dexmedetomidine in young (18–40 years), middle age (41–65 years), and elderly (>65 years) subjects.

Patients with Hepatic Impairment

In adult subjects with varying degrees of hepatic impairment (Child-Pugh Class A, B, or C), clearance values for dexmedetomidine were lower than in healthy subjects. The mean clearance values for patients with mild, moderate, and severe hepatic impairment were 74%, 64% and 53% of those observed in the normal healthy adult subjects, respectively. Mean clearances for free drug were 59%, 51% and 32% of those observed in the normal healthy adult subjects, respectively.

Although dexmedetomidine is dosed to effect, it may be necessary to consider dose reduction in subjects with hepatic impairment [see Dosage and Administration (2.2), Warnings and Precautions (5.8)].

Patients with Renal Impairment

Dexmedetomidine pharmacokinetics (Cmax, Tmax, AUC, t1/2, CL, and Vss) were not significantly different in patients with severe renal impairment (creatinine clearance: <30 mL/min) compared to healthy subjects.

Drug Interaction Studies

In Vitro Studies: In vitro studies in human liver microsomes demonstrated no evidence of cytochrome P450 mediated drug interactions that are likely to be of clinical relevance.

13 NONCLINICAL TOXICOLOGY

13.1 Carcinogenesis, Mutagenesis, Impairment of Fertility

Carcinogenesis

Animal carcinogenicity studies have not been performed with dexmedetomidine.

Mutagenesis

Dexmedetomidine was not mutagenic in vitro, in either the bacterial reverse mutation assay (E. coli and Salmonella typhimurium) or the mammalian cell forward mutation assay (mouse lymphoma). Dexmedetomidine was clastogenic in the in vitro human lymphocyte chromosome aberration test with, but not without, rat S9 metabolic activation. In contrast, dexmedetomidine was not clastogenic in the in vitro human lymphocyte chromosome aberration test with or without human S9 metabolic activation. Although dexmedetomidine was clastogenic in an in vivo mouse micronucleus test in NMRI mice, there was no evidence of clastogenicity in CD-1 mice.

Impairment of Fertility

Fertility in male or female rats was not affected after daily subcutaneous injections of dexmedetomidine at doses up to 54 mcg/kg (less than the maximum recommended human intravenous dose on a mcg/m^2 basis) administered from 10 weeks prior to mating in males, and 3 weeks prior to mating and during mating in females.

13.2 Animal Pharmacology and/or Toxicology

There were no differences in the adrenocorticotropic hormone (ACTH)-stimulated cortisol response in dogs following a single dose of dexmedetomidine compared to saline control. However, after continuous subcutaneous infusions of dexmedetomidine at 3 mcg/kg/hour and 10 mcg/kg/hour for one week in dogs (exposures estimated to be within the clinical range), the ACTH-stimulated cortisol response was diminished by approximately 27% and 40%, respectively, compared to saline-treated control animals indicating a dose-dependent adrenal suppression.

14 CLINICAL STUDIES

The safety and efficacy of dexmedetomidine has been evaluated in four randomized, double-blind, placebo-controlled multicenter clinical trials in 1,185 adult patients.

14.1 Intensive Care Unit Sedation

Two randomized, double-blind, parallel-group, placebo-controlled multicenter clinical trials included 754 adult patients being treated in a surgical intensive care unit. All patients were initially intubated and received mechanical ventilation. These trials evaluated the sedative properties of dexmedetomidine by comparing the amount of rescue medication (midazolam in one trial and propofol in the second) required to achieve a specified level of sedation (using the standardized Ramsay Sedation Scale) between dexmedetomidine and placebo from onset of treatment to extubation or to a total treatment duration of 24 hours. The Ramsay Level of Sedation Scale is displayed in Table 9.

Table 9: Ramsay Level of Sedation Scale

Clinical Score | Level of Sedation Achieved
6 | Asleep, no response
5 | Asleep, sluggish response to light glabellar tap or loud auditory stimulus
4 | Asleep, but with brisk response to light glabellar tap or loud auditory stimulus
3 | Patient responds to commands
2 | Patient cooperative, oriented, and tranquil
1 | Patient anxious, agitated, or restless

In the first study, 175 adult patients were randomized to receive placebo and 178 to receive dexmedetomidine by intravenous infusion at a dose of 0.4 mcg/kg/hr (with allowed adjustment between 0.2 and 0.7 mcg/kg/hr) following an initial loading infusion of one mcg/kg intravenous over 10 minutes. The study drug infusion rate was adjusted to maintain a Ramsay sedation score of ≥3. Patients were allowed to receive “rescue” midazolam as needed to augment the study drug infusion. In addition, morphine sulfate was administered for pain as needed. The primary outcome measure for this study was the total amount of rescue medication (midazolam) needed to maintain sedation as specified while intubated. Patients randomized to placebo received significantly more midazolam than patients randomized to dexmedetomidine (see Table 10).

A second prospective primary analysis assessed the sedative effects of dexmedetomidine by comparing the percentage of adult patients who achieved a Ramsay sedation score of ≥3 during intubation without the use of additional rescue medication. A significantly greater percentage of adult patients in the dexmedetomidine group maintained a Ramsay sedation score of ≥3 without receiving any midazolam rescue compared to the placebo group (see Table 10).

Table 10: Midazolam Use as Rescue Medication During Intubation (ITT) Study One

 | Placebo (N = 175) | Dexmedetomidine (N = 178) | p-value
Mean Total Dose (mg) of Midazolam | 19 mg | 5 mg | 0.0011*
Standard deviation | 53 mg | 19 mg
Categorized Midazolam Use
0 mg | 43 (25%) | 108 (61%) | <0.001**
0–4 mg | 34 (19%) | 36 (20%)
>4 mg | 98 (56%) | 34 (19%)
ITT (intent-to-treat) population includes all randomized patients.
* ANOVA model with treatment center.
** Chi-square.

A prospective secondary analysis assessed the dose of morphine sulfate administered to adult patients in the dexmedetomidine and placebo groups. On average, dexmedetomidine-treated patients received less morphine sulfate for pain than placebo-treated patients (0.47 versus 0.83 mg/h). In addition, 44% (79 of 178 patients) of dexmedetomidine patients received no morphine sulfate for pain versus 19% (33 of 175 patients) in the placebo group.

In a second study, 198 adult patients were randomized to receive placebo and 203 to receive dexmedetomidine by intravenous infusion at a dose of 0.4 mcg/kg/hr (with allowed adjustment between 0.2 and 0.7 mcg/kg/hr) following an initial loading infusion of one mcg/kg intravenous over 10 minutes. The study drug infusion was adjusted to maintain a Ramsay sedation score of ≥3. Patients were allowed to receive “rescue” propofol as needed to augment the study drug infusion. In addition, morphine sulfate was administered as needed for pain. The primary outcome measure for this study was the total amount of rescue medication (propofol) needed to maintain sedation as specified while intubated.

Adult patients randomized to placebo received significantly more propofol than adult patients randomized to dexmedetomidine (see Table 11).

A significantly greater percentage of adult patients in the dexmedetomidine group compared to the placebo group maintained a Ramsay sedation score of ≥3 without receiving any propofol rescue (see Table 11).

Table 11: Propofol Use as Rescue Medication During Intubation (ITT) Study Two

 | Placebo (N = 198) | Dexmedetomidine (N = 203) | p-value
Mean Total Dose (mg) of Propofol | 513 mg | 72 mg | <0.0001*
Standard deviation | 782 mg | 249 mg
Categorized Propofol Use
0 mg | 47 (24%) | 122 (60%) | <0.001**
0–50 mg | 30 (15%) | 43 (21%)
>50 mg | 121 (61%) | 38 (19%)
* ANOVA model with treatment center.
** Chi-square.

A prospective secondary analysis assessed the dose of morphine sulfate administered to adult patients in the dexmedetomidine and placebo groups. On average, dexmedetomidine-treated patients received less morphine sulfate for pain than placebo-treated patients (0.43 versus 0.89 mg/h). In addition, 41% (83 of 203 patients) of dexmedetomidine patients received no morphine sulfate for pain versus 15% (30 of 198 patients) in the placebo group.

In a controlled clinical trial, dexmedetomidine was compared to midazolam for ICU sedation exceeding 24 hours duration. Dexmedetomidine was not shown to be superior to midazolam for the primary efficacy endpoint, the percent of time patients were adequately sedated (81% versus 81%). In addition, administration of dexmedetomidine for longer than 24 hours was associated with tolerance, tachyphylaxis, and a dose-related increase in adverse events [see Adverse Reactions (6.1)].

14.2 Procedural Sedation

Adult Patients

The safety and efficacy of dexmedetomidine for sedation of non-intubated adult patients prior to and/or during surgical and other procedures was evaluated in two randomized, double-blind, placebo-controlled multicenter clinical trials. Study 1 evaluated the sedative properties of dexmedetomidine in adult patients having a variety of elective surgeries/procedures performed under monitored anesthesia care. Study 2 evaluated dexmedetomidine in adult patients undergoing awake fiberoptic intubation prior to a surgical or diagnostic procedure.

In Study 1, the sedative properties of dexmedetomidine were evaluated by comparing the percent of adult patients not requiring rescue midazolam to achieve a specified level of sedation using the standardized Observer’s Assessment of Alertness/Sedation Scale (see Table 12).

Table 12: Observer’s Assessment of Alertness/Sedation
Assessment Categories
Responsiveness | Speech | Facial Expression | Eyes | Composite Score
Responds readily to name spoken in normal tone | Normal | Normal | Clear, no ptosis | 5 (alert)
Lethargic response to name spoken in normal tone | Mild slowing or thickening | Mild relaxation | Glazed or mild ptosis (less than half the eye) | 4
Responds only after name is called loudly and/or repeatedly | Slurring or prominent slowing | Marked relaxation (slack jaw) | Glazed and marked ptosis (half the eye or more) | 3
Responds only after mild prodding or shaking | Few recognizable words | – | – | 2
Does not respond to mild prodding or shaking | – | – | – | 1 (deep sleep)

Adult patients were randomized to receive a loading infusion of either dexmedetomidine 1 mcg/kg, dexmedetomidine 0.5 mcg/kg, or placebo (normal saline) given over 10 minutes and followed by a maintenance infusion started at 0.6 mcg/kg/hr. The maintenance infusion of study drug could be titrated from 0.2 mcg/kg/hr to 1 mcg/kg/hr to achieve the targeted sedation score (Observer’s Assessment of Alertness/Sedation Scale ≤4). Adult patients were allowed to receive rescue midazolam as needed to achieve and/or maintain an Observer’s Assessment of Alertness/Sedation Scale ≤4. After achieving the desired level of sedation, a local or regional anesthetic block was performed. Demographic characteristics were similar between the dexmedetomidine and comparator groups. Efficacy results showed that dexmedetomidine was more effective than the comparator group when used to sedate non-intubated patients requiring monitored anesthesia care during surgical and other procedures (see Table 13).

In Study 2, the sedative properties of dexmedetomidine were evaluated by comparing the percent of adult patients requiring rescue midazolam to achieve or maintain a specified level of sedation using the Ramsay Sedation Scale score ≥2 (see Table 9). Adult patients were randomized to receive a loading infusion of dexmedetomidine 1 mcg/kg or placebo (normal saline) given over 10 minutes and followed by a fixed maintenance infusion of 0.7 mcg/kg/hr. After achieving the desired level of sedation, topicalization of the airway occurred. Adult patients were allowed to receive rescue midazolam as needed to achieve and/or maintain a Ramsay Sedation Scale ≥2. Demographic characteristics were similar between the dexmedetomidine and comparator groups. For efficacy results see Table 13.

Table 13: Key Efficacy Results of Adult Procedural Sedation Studies
Study | Loading Infusion Treatment Arm | Number of Patients Enrolleda | % Not Requiring Midazolam Rescue | Confidenceb Interval on the Difference vs. Placebo | Mean (SD) Total Dose (mg) of Rescue Midazolam Required | Confidenceb Intervals of the Mean Rescue Dose
Study 1 | Dexmedetomidine 0.5 mcg/kg | 134 | 40 | 37 (27, 48) | 1.4 (1.7) | -2.7; (-3.4, -2.0)
Study 1 | Dexmedetomidine 1 mcg/kg | 129 | 54 | 51 (40, 62) | 0.9 (1.5) | -3.1; (-3.8, -2.5)
Study 1 | Placebo | 63 | 3 | – | 4.1 (3.0) | –
Study 2 | Dexmedetomidine 1 mcg/kg | 55 | 53 | 39 (20, 57) | 1.1 (1.5) | -1.8; (-2.7, -0.9)
Study 2 | Placebo | 50 | 14 | – | 2.9 (3.0) | –

a Based on ITT population defined as all randomized and treated patients.

b Normal approximation to the binomial with continuity correction

16 HOW SUPPLIED/STORAGE AND HANDLING

Dexmedetomidine Injection is clear and colorless, and is available in a 100 mcg/mL strength in clear glass, multiple-dose vials as follows:

NDC No. | Strength | Package
44567-600-04 | 400 mcg/4 mL | 4 vials/carton
44567-601-04 | 1000 mcg/10 mL | 4 vials/carton

Store vials at 20℃ to 25°C (68℉ to 77°F); excursions permitted 15℃ to 30°C (59℉ to 86°F) [see USP Controlled Room Temperature].

Dexmedetomidine in 5% Dextrose Injection is available in a 4 mcg/mL strength in single-dose, single-port, flexible plastic ready-to-use infusion bags in a foil laminate overwrap as follows:

NDC No. | Strength | Package
44567-602-24 | 200 mcg/50 mL | 24 bags/carton
44567-603-24 | 400 mcg/100 mL | 24 bags/carton

Store bags at 20℃ to 25°C (68℉ to 77°F); excursions permitted 15℃ to 30°C (59℉ to 86°F) [see USP Controlled Room Temperature]. Protect from light. It is recommended that the infusion bags be kept in the overwrap until ready to use. PROTECT INFUSION BAGS FROM FREEZING.

17 PATIENT COUNSELING INFORMATION

Dexmedetomidine is indicated for short-term intravenous sedation. Dosage must be individualized and titrated to the desired clinical effect. Blood pressure, heart rate and oxygen levels will be monitored both continuously during the infusion of dexmedetomidine and as clinically appropriate after discontinuation.

- When dexmedetomidine is infused for more than 6 hours, patients should be informed to report nervousness, agitation, and headaches that may occur for up to 48 hours.
- Additionally, patients should be informed to report symptoms that may occur within 48 hours after the administration of dexmedetomidine such as: weakness, confusion, excessive sweating, weight loss, abdominal pain, salt cravings, diarrhea, constipation, dizziness or light-headedness.
- Advise breastfeeding mothers who were exposed to dexmedetomidine to monitor breastfed neonates for irritability [see Use in Specific Populations (8.2)].

Manufactured for:

WG Critical Care, LLC

Paramus, NJ 07652

Vials made in Finland

Bags made in Switzerland

U.S. Patent Numbers 9,649,296 and 9,717,796

PRINCIPAL DISPLAY PANEL

NDC 44567-600-04

Dexmedetomidine Injection

400 mcg/4 mL (100 mcg/mL)

Rx only WG Critical Care

PRINCIPAL DISPLAY PANEL

NDC 44567-601-04

Dexmedetomidine Injection

1000 mcg/10 mL (100 mcg/mL)

Rx only WG Critical Care

Package/Label Display Panel

NDC 44567-602-24 Rx only

Dexmedetomidine

in 5% Dextrose Injection

200 mcg/50 mL (4 mcg/mL)

For Intravenous Use Only

Package/Label Display Panel

NDC 44567-603-24 Rx only

Dexmedetomidine

in 5% Dextrose Injection

400 mcg/100 mL (4 mcg/mL)

For Intravenous Use Only